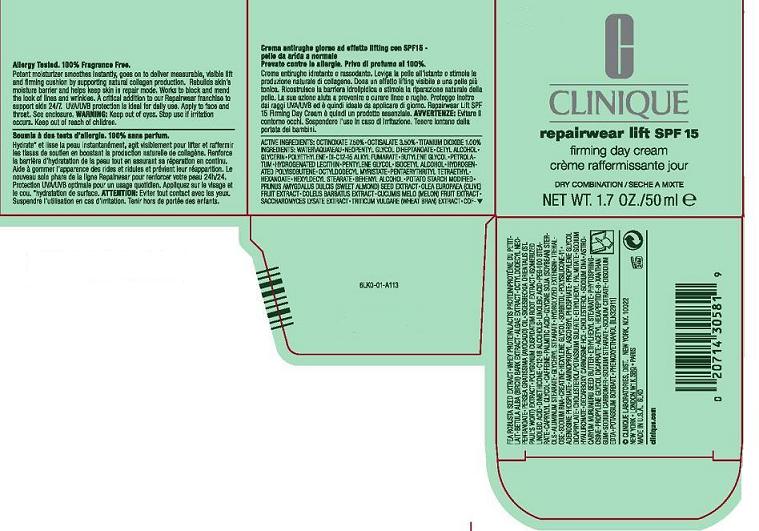 DRUG LABEL: REPAIRWEAR LIFT
NDC: 49527-719 | Form: CREAM
Manufacturer: CLINIQUE LABORATORIES INC
Category: otc | Type: HUMAN OTC DRUG LABEL
Date: 20110725

ACTIVE INGREDIENTS: OCTINOXATE 7.5 mL/100 mL; OCTISALATE 3.5 mL/100 mL; TITANIUM DIOXIDE 1.0 mL/100 mL
INACTIVE INGREDIENTS: WATER; NEOPENTYL GLYCOL DIHEPTANOATE; CETYL ALCOHOL; GLYCERIN; DI-C12-15 ALKYL FUMARATE; PETROLATUM; HYDROGENATED SOYBEAN LECITHIN; BUTYLENE GLYCOL; PENTYLENE GLYCOL; ISOCETYL ALCOHOL; HYDROGENATED POLYBUTENE (1300 MW); OCTYLDODECYL MYRISTATE; DOCOSANOL; STARCH, POTATO; ALMOND; OLIVE OIL; PLECTRANTHUS BARBATUS ROOT; CUCUMBER; SACCHAROMYCES LYSATE; WHEAT GERM; ROBUSTA COFFEE BEAN; WHEY; BETULA PUBESCENS BARK; SEAWEED; OCTYLDODECYL NEOPENTANOATE; AVOCADO OIL; POLYGONUM CUSPIDATUM ROOT; LINOLEIC ACID; DIMETHICONE; C12-16 ALCOHOLS; PEG-100 STEARATE; CAPRYLYL GLYCOL; CAFFEINE; PALMITIC ACID; ALUMINUM STEARATE; GLYCERYL MONOSTEARATE; TREHALOSE; CREATINE; HEXYLENE GLYCOL; SORBITOL; ADENOSINE PHOSPHATE; PROPYLENE GLYCOL DICAPRYLATE; ETHYLHEXYL PALMITATE; HYALURONATE SODIUM; CHOLESTEROL; ASTROCARYUM MURUMURU SEED BUTTER; ETHYLHEXYL STEARATE; PROPYLENE GLYCOL DICAPRATE; ACETYL HEXAPEPTIDE-3; XANTHAN GUM; SODIUM STEARATE; SODIUM CITRATE; EDETATE DISODIUM; POTASSIUM SORBATE; PHENOXYETHANOL

ACTIVE INGREDIENT

active ingredients: octinoxate 7.50% [] octisalate 3.50% [] titanium dioxide 1.00%

INACTIVE INGREDIENT

inactive ingredients: water [] neopentyl glycol diheptanoate [] cetyl alcohol [] glycerin [] polyethylene [] di-c12-15 alkyl fumarate [] petrolatum [] hydrogenated lecithin [] butylene glycol [] pentylene glycol [] isocetyl alcohol [] hydrogenated polyisobutene [] octyldodecyl myristate [] pentaerythrityl tetraethylhexanoate [] hexyldecyl stearate [] behenyl alcohol [] potato starch modified [] prunus amygdalus dulcis (sweet almond) seed extract [] olea europaea (olive) fruit extract [] coleus barbatus extract [] cucumis melo (melon) fruit extract [] saccharomyces lysate extract [] triticum vulgare (wheat bran) extract [] coffea robusta seed extract [] whey protein\lactis protein\protéine du petit-lait [] betula alba (birch) bark extract [] algae extract [] octyldodecyl neopentanoate [] persea gratissima (avocado) oil [] sigesbeckia orientalis (st. paul's wort) extract [] polygonum cuspidatum root extract [] thermus thermophillus ferment [] isomerized linoleic acid [] dimethicone [] c12-16 alcohols [] linoleic acid [] peg-100 stearate [] caprylyl glycol [] caffeine [] palmitic acid [] glycine soja (soybean) sterols [] aluminum stearate [] glyceryl stearate [] trehalose [] sodium rna [] creatine [] hexylene glycol [] sorbitol [] polysilicone-11 [] adenosine phosphate [] aminopropyl ascorbyl phosphate [] propylene glycol dicaprylate [] cholesterol/potassium sulfate [] ethylhexyl palmitate [] sodium hyaluronate [] decarboxy carnosine hcl [] cholesterol [] sodium dna [] astrocaryum murumuru seed butter [] ethylhexyl stearate [] phytosphingosine [] propylene glycol dicaprate [] acetyl hexapeptide-8 [] xanthan gum [] sodium stearate [] sodium carbomer [] sodium citrate [] disodium edta [] potassium sorbate [] phenoxyethanol

WARNINGS

warning: keep out of eyes. stop use if irritation occurs. keep out of reach of children.

PACKAGE LABEL

principal display panel:

CLINIQUE

REPAIRWEAR LIFT SPF 15

FIRMING DAY CREAM

DRY COMBINATION SKIN

1.7 OZ/ 50 ML

CLINIQUE LABORATORIES DISTR.

NEW YORK, NY 10022